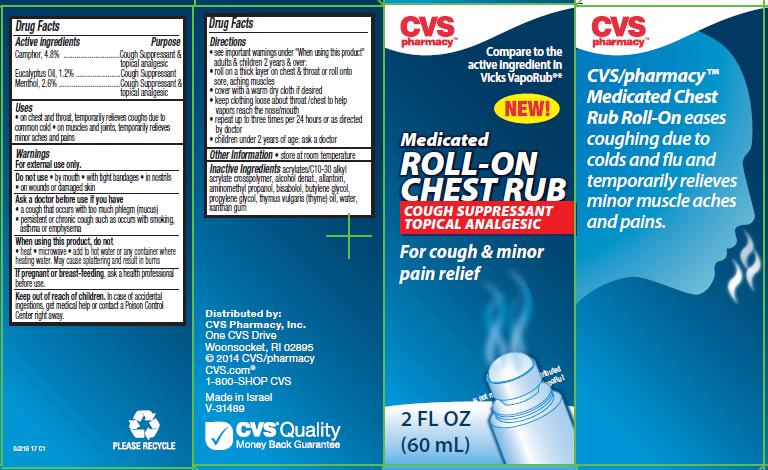 DRUG LABEL: CVS Medicated Chest Rub Roll-On
NDC: 59779-613 | Form: GEL
Manufacturer: CVS Pharmacy
Category: otc | Type: HUMAN OTC DRUG LABEL
Date: 20140910

ACTIVE INGREDIENTS: CAMPHOR (NATURAL) 4.8 g/100 mL; EUCALYPTUS OIL 1.2 g/100 mL; MENTHOL 2.6 g/100 mL
INACTIVE INGREDIENTS: CARBOMER INTERPOLYMER TYPE A (ALLYL SUCROSE CROSSLINKED); ALCOHOL; ALLANTOIN; AMINOMETHYLPROPANOL; LEVOMENOL; BUTYLENE GLYCOL; PROPYLENE GLYCOL; THYME OIL; WATER; XANTHAN GUM

CVS pharmacy™ Medicated ROLL-ON CHEST RUB

Active ingredient

Camphor, 4.8%
Eucalyptus Oil, 1.2%
Menthol, 2.6%

Purpose

Cough Suppressant & topical analgesic
Cough Suppressant
Cough Suppressant & topical analgesic

Uses

- on chest and throat, temporarily relieves coughs due to common cold
- on muscles and joints, temporarily relieves minor aches and pains

Warnings

For external use only.

Do not use

- by mouth
- with tight bandages
- in nostrils
- on wounds or damaged skin

Ask a doctor before use if you have

- a cough that occurs with too much phlegm (mucus)
- persistent or chronic cough such as occurs with smoking, asthma or emphysema

When using this product, do not

- heat
- microwave
- add to hot water or any container where heating water. May cause splattering and result in burns

If pregnant or breast-feeding,

ask a health professional before use.

Keep out of reach of children.

In case of accidental ingestions, get medical help or contact a Poison Control Center right away.

Directions

- see important warnings under “When using this product”
  adults & children 2 years & over:
- roll on a thick layer on chest & throat or roll onto sore, aching muscles
- cover with a warm dry cloth if desired
- keep clothing loose about throat/chest to help vapors reach the nose/mouth
- repeat up to three times per 24 hours or as directed by doctor
- children under 2 years of age: ask a doctor

Other Information

- store at room temperature

Inactive Ingredients

acrylates/C10-30 alkyl acrylate crosspolymer, alcohol denat., allantoin, aminomethyl propanol, bisabolol, butylene glycol, propylene glycol, thymus vulgaris (thyme) oil, water, xanthan gum

Package/Label Principal Display Panel

CVS
pharmacy™

Compare to the
active ingredient in
Vicks VapoRub®*

NEW!
Medicated
ROLL-ON
CHEST RUB
COUGH SUPPRESSANT
TOPICAL ANALGESIC

For cough & minor
pain relief

2 FL OZ
(60 mL)

CVS/pharmacy™
Medicated Chest
Rub Roll-On eases
coughing due to
colds and flu and
temporarily relieves
minor muscle aches
and pains.

Distributed by:
CVS Pharmacy, Inc.
One CVS Drive
Woonsocket, RI 02895
© 2014 CVS/pharmacy
CVS.com®
1-800-SHOP CVS

Made in Israel
V-31489

CVS® Quality
Money Back Guarantee

0J216 17 C1

Carton Label